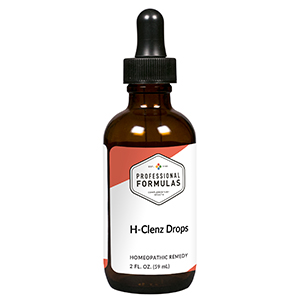 DRUG LABEL: H-Clenz Drops
NDC: 63083-2026 | Form: LIQUID
Manufacturer: Professional Complementary Health Formulas
Category: homeopathic | Type: HUMAN OTC DRUG LABEL
Date: 20190815

ACTIVE INGREDIENTS: CASSAVA 3 [hp_X]/59 mL; FRANGULA PURSHIANA BARK 3 [hp_X]/59 mL; DIOSCOREA VILLOSA TUBER 6 [hp_X]/59 mL; STRYCHNOS NUX-VOMICA SEED 6 [hp_X]/59 mL; ALUMINUM OXIDE 12 [hp_X]/59 mL; SULFUR 12 [hp_X]/59 mL; LYCOPODIUM CLAVATUM SPORE 30 [hp_X]/59 mL
INACTIVE INGREDIENTS: ALCOHOL; WATER

C26

ACTIVE INGREDIENTS

Cassada 3X
Rhamnus purshiana 3X
Dioscorea villosa 6X
Nux vomica 6X
Alumina 12X
Sulphur 12X
Lycopodium clavatum 30X

QUESTIONS

Professional Formulas

PO Box 2034 Lake Oswego, OR 97035

INDICATIONS

For the temporary relief of occasional constipation or bloating.*

PURPOSE

*Claims based on traditional homeopathic practice, not accepted medical evidence. Not FDA evaluated.

WARNINGS

Consult a doctor if condition worsens or if symptoms persist. Keep out of the reach of children. In case of overdose, get medical help or contact a poison control center right away. If pregnant or breastfeeding, ask a healthcare professional before use.

Keep out of the reach of children.

PREGNANCY OR BREAST FEEDING

If pregnant or breastfeeding, ask a healthcare professional before use.

DIRECTIONS

Place drops under tongue 30 minutes before/after meals. Adults and children 12 years and over: Take 10 drops up to 3 times per day. Consult a physician for use in children under 12 years of age.

OTHER INFORMATION

Tamper resistant. If seal is broken, do not use. After opening, close container tightly and store at room temperature away from heat.

INACTIVE INGREDIENTS

20% ethanol, purified water.

LABEL

Est 1985

Professional Formulas

Complementary Health

H-Clenz Drops

Homeopathic Remedy

2 FL. OZ. (59 mL)